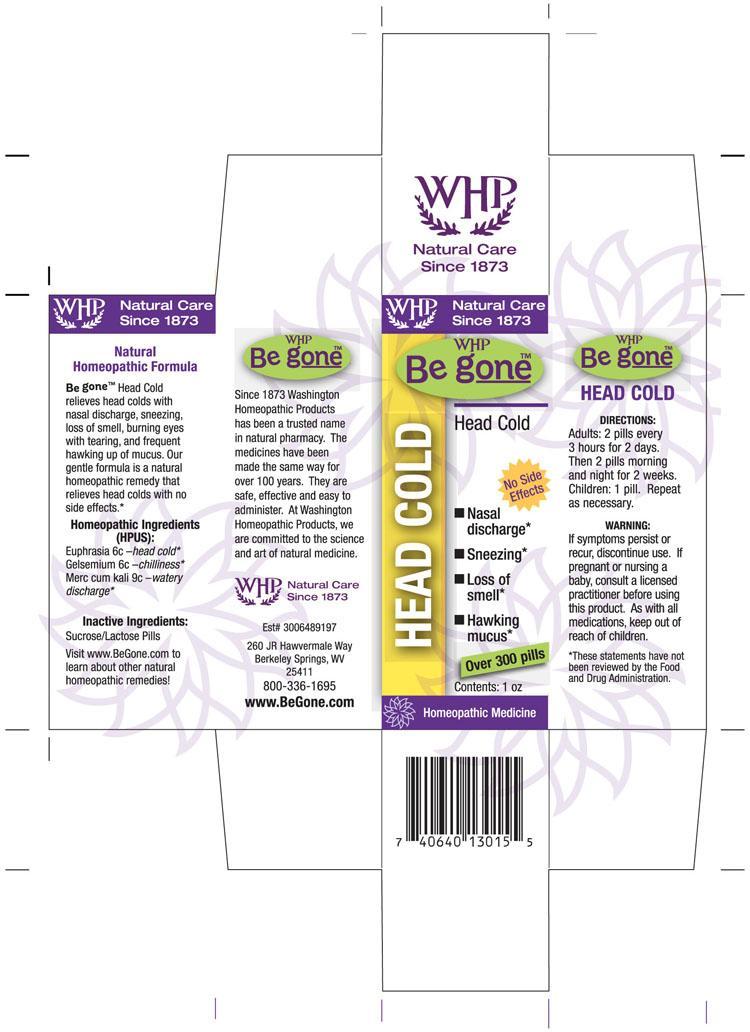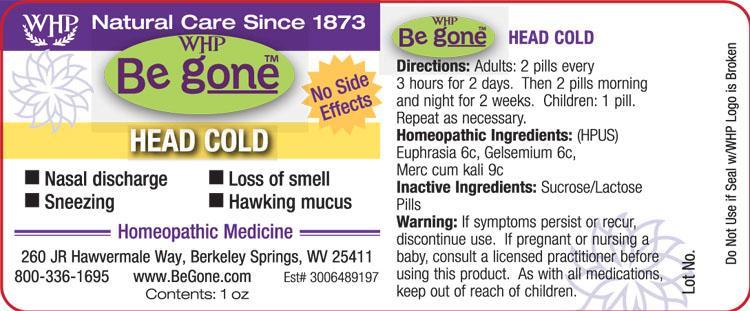 DRUG LABEL: WHP Be gone Head Cold
NDC: 68428-742 | Form: PELLET
Manufacturer: Washington Homeopathic Products
Category: homeopathic | Type: HUMAN OTC DRUG LABEL
Date: 20130913

ACTIVE INGREDIENTS: POTASSIUM MERCURIC IODIDE 6 [hp_C]/28 g; GELSEMIUM SEMPERVIRENS ROOT 6 [hp_C]/28 g; EUPHRASIA STRICTA 6 [hp_C]/28 g
INACTIVE INGREDIENTS: SUCROSE; LACTOSE

DRUG FACTS

ACTIVE INGREDIENTS

EUPHRASIA 6C

GELSEMIUM 6C

MERC CUM KALI 9C

USES

Relieves head colds with nasal discharge, sneezing, loss of smell, burning eyes with tearing, frequent hawking up of mucus.

KEEP OUT OF REACH OF CHILDREN

As with all medications, keep out of reach of children.

INDICATIONS

EUPHRASIA head cold

GELSEMIUM chilliness

MERC CUM KALI watery discharge

STOP USE AND ASK DOCTOR

If symptoms persist or recur, discontinue use. If pregnant or nursing a baby, consult a licensed practitioner before using this product.

DIRECTIONS

Adults 2 pills every 3 hours for 2 days. Then 2 pills morning and night for 2 weeks.

Children: 1 pills. Repeat as necessary.

INACTIVE INGREDIENTS

Sucrose/Lactose

PRINCIPAL DISPLAY PANEL

WHP Be goneTM Head Cold label

WHP Be goneTM Head Cold box